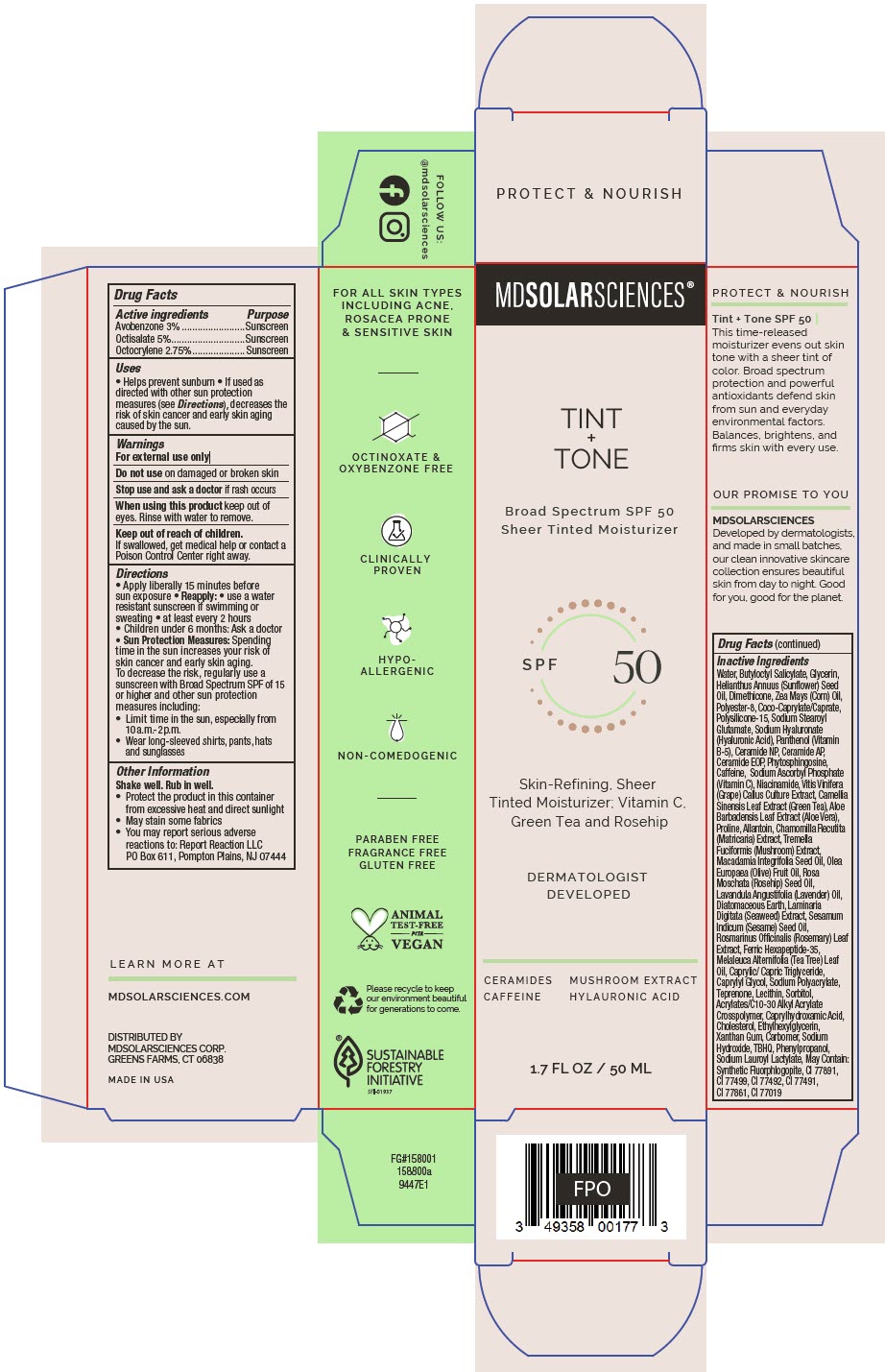 DRUG LABEL: Tint plus Tone SPF 50.
NDC: 49358-582 | Form: LOTION
Manufacturer: MDSolarSciences
Category: otc | Type: HUMAN OTC DRUG LABEL
Date: 20250605

ACTIVE INGREDIENTS: AVOBENZONE 30 mg/1 mL; OCTISALATE 50 mg/1 mL; OCTOCRYLENE 27.5 mg/1 mL
INACTIVE INGREDIENTS: WATER; BUTYLOCTYL SALICYLATE; GLYCERIN; HELIANTHUS ANNUUS FLOWERING TOP; DIMETHICONE; CORN OIL; POLYESTER-8 (1400 MW, CYANODIPHENYLPROPENOYL CAPPED); COCOYL CAPRYLOCAPRATE; POLYSILICONE-15; SODIUM STEAROYL GLUTAMATE; HYALURONATE SODIUM; PANTHENOL; CERAMIDE NP; CERAMIDE AP; CERAMIDE 9; PHYTOSPHINGOSINE; CAFFEINE; SODIUM ASCORBYL PHOSPHATE; NIACINAMIDE; VITIS VINIFERA SEED; GREEN TEA LEAF; ALOE VERA LEAF; PROLINE; ALLANTOIN; CHAMOMILE; TREMELLA FUCIFORMIS FRUITING BODY; MACADAMIA OIL; OLIVE OIL; ROSA MOSCHATA SEED OIL; LAVENDER OIL; DIATOMACEOUS EARTH; LAMINARIA DIGITATA; SESAME OIL; ROSEMARY; ACETYL HEXAPEPTIDE-8; TEA TREE OIL; MEDIUM-CHAIN TRIGLYCERIDES; CAPRYLYL GLYCOL; SODIUM POLYACRYLATE (8000 MW); TEPRENONE; HYDROGENATED SOYBEAN LECITHIN; SORBITOL; CARBOMER INTERPOLYMER TYPE A (ALLYL SUCROSE CROSSLINKED); CAPRYLHYDROXAMIC ACID; CHOLESTEROL; ETHYLHEXYLGLYCERIN; XANTHAN GUM; CARBOMER HOMOPOLYMER TYPE C (ALLYL PENTAERYTHRITOL CROSSLINKED); SODIUM LAUROYL LACTYLATE; TERT-BUTYLHYDROQUINONE; PHENYLPROPANOL

Tint + Tone SPF 50.
SPF 50 Broad Spectrum Sunscreen Sheer Tinted Moisturizer

Drug Facts

ACTIVE INGREDIENT

Active ingredients | Purpose
Avobenzone 3% | Sunscreen
Octisalate 5% | Sunscreen
Octocrylene 2.75% | Sunscreen

Uses

- Helps prevent sunburn
- If used as directed with other sun protection measures (see Directions), decreases the risk of skin cancer and early skin aging caused by the sun.

Warnings

For external use only

Do not useon damaged or broken skin

Stop use and ask a doctorif rash occurs

WHEN USING

When using this productkeep out of eyes. Rinse with water to remove.

Keep out of reach of children.

If swallowed, get medical help or contact a Poison Control Center right away.

Directions

- Apply liberally 15 minutes before sun exposure
- Reapply:
  - use a water resistant sunscreen if swimming or sweating
  - at least every 2 hours
- Children under 6 months: Ask a doctor
- Sun Protection Measures:Spending time in the sun increases your risk of skin cancer and early skin aging. To decrease the risk, regularly use a sunscreen with Broad Spectrum SPF of 15 or higher and other sun protection measures including:
  - Limit time in the sun, especially from 10a.m.-2p.m.
  - Wear long-sleeved shirts, pants, hats and sunglasses

Other Information

Shake well. Rub in well.

- Protect the product in this container from excessive heat and direct sunlight
- May stain some fabrics
- You may report serious adverse reactions to: Report Reaction LLC
  PO Box 611, Pompton Plains, NJ 07444

Inactive Ingredients

Water, Butyloctyl Salicylate, Glycerin, Helianthus Annuus (Sunflower) Seed Oil, Dimethicone, Zea Mays (Corn) Oil, Polyester-8, Coco-Caprylate/Caprate, Polysilicone-15, Sodium Stearoyl Glutamate, Sodium Hyaluronate (Hyaluronic Acid), Panthenol (Vitamin B-5), Ceramide NP, Ceramide AP, Ceramide EOP, Phytosphingosine, Caffeine, Sodium Ascorbyl Phosphate (Vitamin C), Niacinamide, Vitis Vinifera (Grape) Callus Culture Extract, Camellia Sinensis Leaf Extract (Green Tea), Aloe Barbadensis Leaf Extract (Aloe Vera), Proline, Allantoin, Chamomilla Recutita (Matricaria) Extract, Tremella Fuciformis (Mushroom) Extract, Macadamia Integrifolia Seed Oil, Olea Europaea (Olive) Fruit Oil, Rosa Moschata (Rosehip) Seed Oil, Lavandula Angustifolia (Lavender) Oil, Diatomaceous Earth, Laminaria Digitata (Seaweed) Extract, Sesamum Indicum (Sesame) Seed Oil, Rosmarinus Officinalis (Rosemary) Leaf Extract, Ferric Hexapeptide-35, Melaleuca Alternifolia (Tea Tree) Leaf Oil, Caprylic/ Capric Triglyceride, Caprylyl Glycol, Sodium Polyacrylate, Teprenone, Lecithin, Sorbitol, Acrylates/C10-30 Alkyl Acrylate Crosspolymer, Caprylhydroxamic Acid, Cholesterol, Ethylhexylglycerin, Xanthan Gum, Carbomer, Sodium Hydroxide, TBHQ, Phenylpropanol, Sodium Lauroyl Lactylate, May Contain: Synthetic Fluorphlogopite, CI 77891, CI 77499, CI 77492, CI 77491, CI 77861, CI 77019

DISTRIBUTED BY
MDSOLARSCIENCES CORP.
GREENS FARMS, CT 06838

PRINCIPAL DISPLAY PANEL - 50 mL Bottle Carton

MDSOLARSCIENCES®

TINT
+
TONE

Broad Spectrum SPF 50
Sheer Tinted Moisturizer

SPF 50

Skin-Refining, Sheer
Tinted Moisturizer; Vitamin C,
Green Tea and Rosehip

DERMATOLOGIST
DEVELOPED

CERAMIDES
CAFFEINE

MUSHROOM EXTRACT
HYLAURONIC ACID

1.7 FL OZ / 50 ML